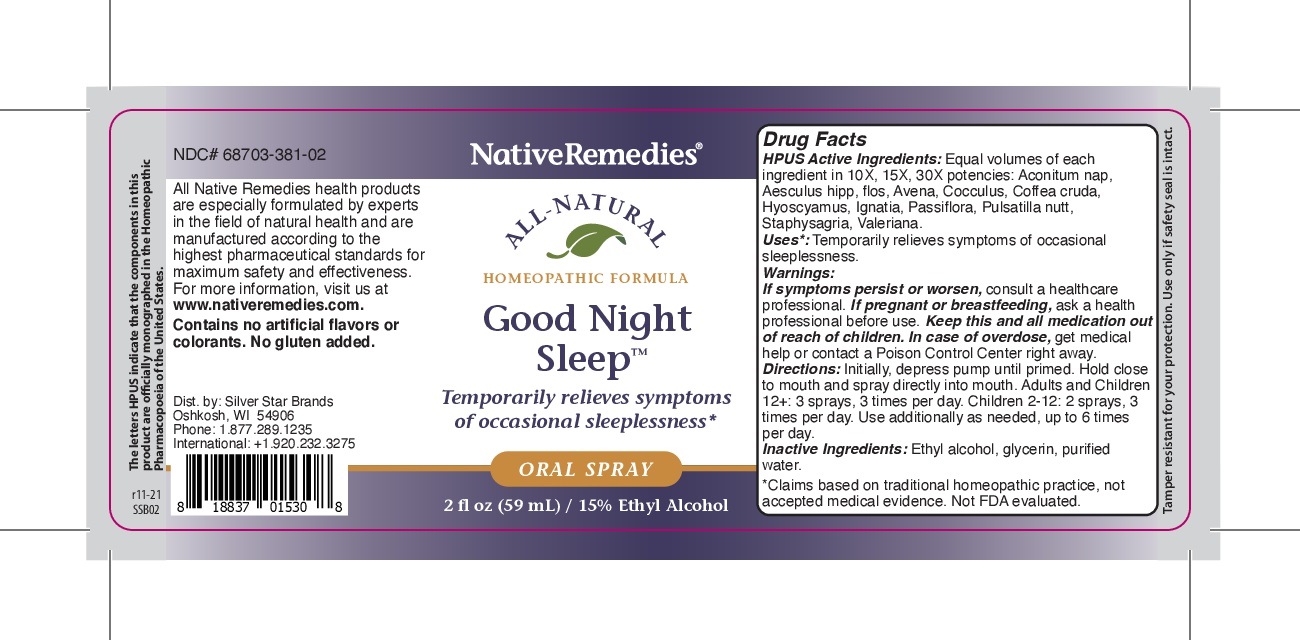 DRUG LABEL: Good Night Sleep
NDC: 68703-381 | Form: SPRAY
Manufacturer: Silver Star Brands
Category: homeopathic | Type: HUMAN OTC DRUG LABEL
Date: 20220125

ACTIVE INGREDIENTS: ANEMONE NEMOROSA EXTRACT 10 [hp_X]/59 mL; DELPHINIUM STAPHISAGRIA SEED 10 [hp_X]/59 mL; STRYCHNOS IGNATII SEED 10 [hp_X]/59 mL; ACONITUM NAPELLUS 10 [hp_X]/59 mL; COFFEA ARABICA FRUIT 10 [hp_X]/59 mL; HYOSCYAMUS NIGER 10 [hp_X]/59 mL; AESCULUS HIPPOCASTANUM FLOWER 10 [hp_X]/59 mL; PASSIFLORA INCARNATA FLOWER 10 [hp_X]/59 mL; VALERIAN 10 [hp_X]/59 mL; AVENA SATIVA LEAF 10 [hp_X]/59 mL; ANAMIRTA COCCULUS SEED 10 [hp_X]/59 mL
INACTIVE INGREDIENTS: ALCOHOL; GLYCERIN; WATER

NativeRemedies® Good Night Sleep Oral Spray

HPUS Active Ingredients: Equal volumes of each ingredient in 10X, 15X, 30X potencies: Aconitum nap, Aesculus hipp, flos, Avena, Cocculus, coffea cruda, Hyoscyamus, Ignatia, Passiflora, Pulsatilla nutt, Staphysagrai, Valeriana.

Uses*:

Uses*: Temporarily relieves symptoms of occasional sleeplessness.

*Claims based on traditional homeopathic practice, not accepted medical evidence. Not FDA evaluated.

Warnings

If symptoms persist or worsen, consulta healthcare professional. if pregnant or breastfeeding, ask a health professional before use. keep this and all medication out of reach of children. in case of overdose, get medical help or contact a Poison Control Center right away.

Directions

Directions: Intially, depress pump until primed. Hold close to mouth and spray directly into mouth. Adults and children 12+: 3 sprays, 3 times per day. Children 2-12: 2 sprays, 3 times per day. Use additionally as needed, up to 6 times per day.

OTHER SAFETY INFORMATION

Contains no artificial flavors or colorants. No gluten added.

Tamper resistant for your protection. use only if safety seal is intact.

Inactive Ingredients

Inactive Ingredients: Ethyl alcohol, glycerin, purified water.

KEEP OUT OF REACH OF CHILDREN

Keep this and all medication out of reach of children.

PREGNANCY OR BREAST FEEDING

If pregnant or breastfeeding, ask a health professional before use.

PURPOSE

Temporarily relieves symptoms of occasional sleeplessness*

*claims based on traditional homeopathic practice, not accepted medical evidence. Not FDA evaluated.